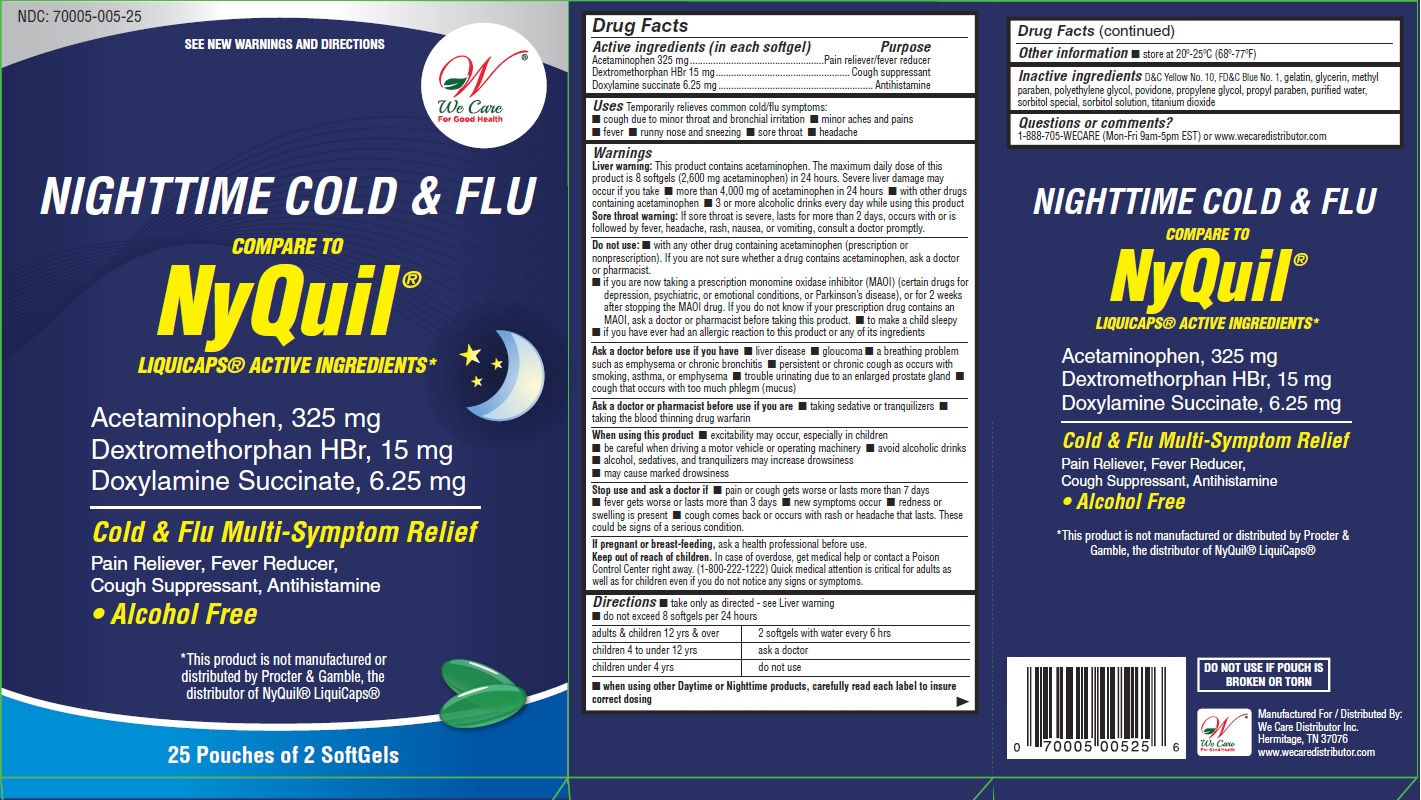 DRUG LABEL: NIGHTTIME COLD AND FLU
NDC: 70005-005 | Form: CAPSULE, LIQUID FILLED
Manufacturer: We Care Distributor Inc.
Category: otc | Type: HUMAN OTC DRUG LABEL
Date: 20160301

ACTIVE INGREDIENTS: ACETAMINOPHEN 325 mg/1 1; DEXTROMETHORPHAN HYDROBROMIDE 15 mg/1 1; DOXYLAMINE SUCCINATE 6.25 mg/1 1
INACTIVE INGREDIENTS: D&C YELLOW NO. 10; FD&C BLUE NO. 1; GELATIN; GLYCERIN; METHYLPARABEN; POLYETHYLENE GLYCOL 1000; POVIDONE; PROPYLENE GLYCOL; PROPYLPARABEN; WATER; SORBITOL; TITANIUM DIOXIDE

NIGHTTIME COLD AND FLU - Acetaminophen, Dextromethorphan HBr and Doxylamine Succinate

Drug Facts

ACTIVE INGREDIENT

Active Ingredient (in each softgel) | Purpose
Acetaminophen 325 mg | Pain reliever/fever reducer
Dextromethorphan HBr 15 mg | Cough suppressant
Doxylamine succinate 6.25 mg | Antihistamine

Uses

Temporarily relieves common cold/flu symptoms:

- cough due to minor throat and bronchial irritation
- minor aches and pains
- fever
- runny nose and sneezing
- sore throat
- headache

Warnings

Liver warning:

This product contains acetaminophen. The maximum daily dose of this product is 8 softgels (2,600 mg acetaminophen) in 24 hours. Severe liver damage may occur if you take

- more than 4,000 mg of acetaminophen in 24 hours
- with other drugs containing acetaminophen
- 3 or more alcoholic drinks every day while using this product

Sore throat warning:

If sore throat is severe, lasts for more than 2 days, occurs with or is followed by fever, headache, rash, nausea, or vomiting, consult a doctor promptly

Do not use

- with any other drug containing acetaminophen (prescription or nonprescription). If you are not sure whether a drug contains acetaminophen, ask a doctor or pharmacist
- if you are now taking a prescription monomine oxidase inhibitor (MAOI) (certain drugs for depression, psychiatric, or emotional conditions, or Parkinson’s disease), or for 2 weeks after stopping the MAOI drug. If you do not know if your prescription drug contains an MAOI, ask a doctor or pharmacist before taking this product.
- to make a child sleepy
- if you have ever had an allergic reaction to this product or any of its ingredients

Ask a doctor before use if you have

- liver disease
- gloucoma
- a breathing problem such as emphysema or chronic bronchitis
- persistent or chronic cough as occurs with smoking, asthma, or emphysema
- trouble urinating due to an enlarged prostate gland
- cough that occurs with too much phlegm (mucus)

Ask a doctor or pharmacist before use if you are

- taking sedative or tranquilizers
- taking the blood thinning drug warfarin

When using this product

- excitability may occur, especially in children
- be careful when driving a motor vehicle or operating machinery
- avoid alcoholic drinks
- alcohol, sedatives, and tranquilizers may increase drowsiness
- may cause marked drowsiness

Stop use and ask a doctor if

- pain or cough gets worse or lasts more than 7 days
- fever gets worse or lasts more than 3 days
- new symptoms occur
- redness or swelling is present
- cough comes back or occurs with rash or headache that lasts

These could be signs of a serious condition.

PREGNANCY OR BREAST FEEDING

If pregnant or breast-feeding, ask a health professional before use.

Keep out of reach of children.

In case of overdose, get medical help or contact a Poison Control Center (1-800-222-1222) right away. Quick medical attention is critical for adults as well as for children even if you do not notice any signs or symptoms.

Directions

- take only as directed - see Liver warning
- do not exceed 8 softgels per 24 hours
- adults and children 12 years and over: 2 softgels with water every 6 hours
- children 4 to under 12 years: ask a doctor
- children under 4 years: do not use
- when using other Daytime or Nighttime products, carefully read each label to insure correct dosing

Other information

- store at 20º-25ºC (68º-77ºF)
- read all product information before using. Keep this box for important information

Inactive ingredients

D&C Yellow No. 10, FD&C Blue No. 1, gelatin, glycerin, methylparaben, polyethylene glycol, povidone, propylene glycol, propylparaben, purified water, sorbitol special, sorbitol solution, titanium dioxide

Questions or comments?

1-888-705-WECARE (Mon-Fri 9am-5pm EST) or www.wecaredistributor.com

PRINCIPAL DISPLAY PANEL

See New Warnings Information & Directions

Compare to the Active Ingredients in

NyQuil® LiquiCaps®

Acetaminophen, Dextromethorphan HBr and Doxylamine Succinate 325 mg, 15 mg and 6.25 mg

TO OPEN
PUSH IN TAB AND PULL OUT

25 Pouches of 2 Softgels Each